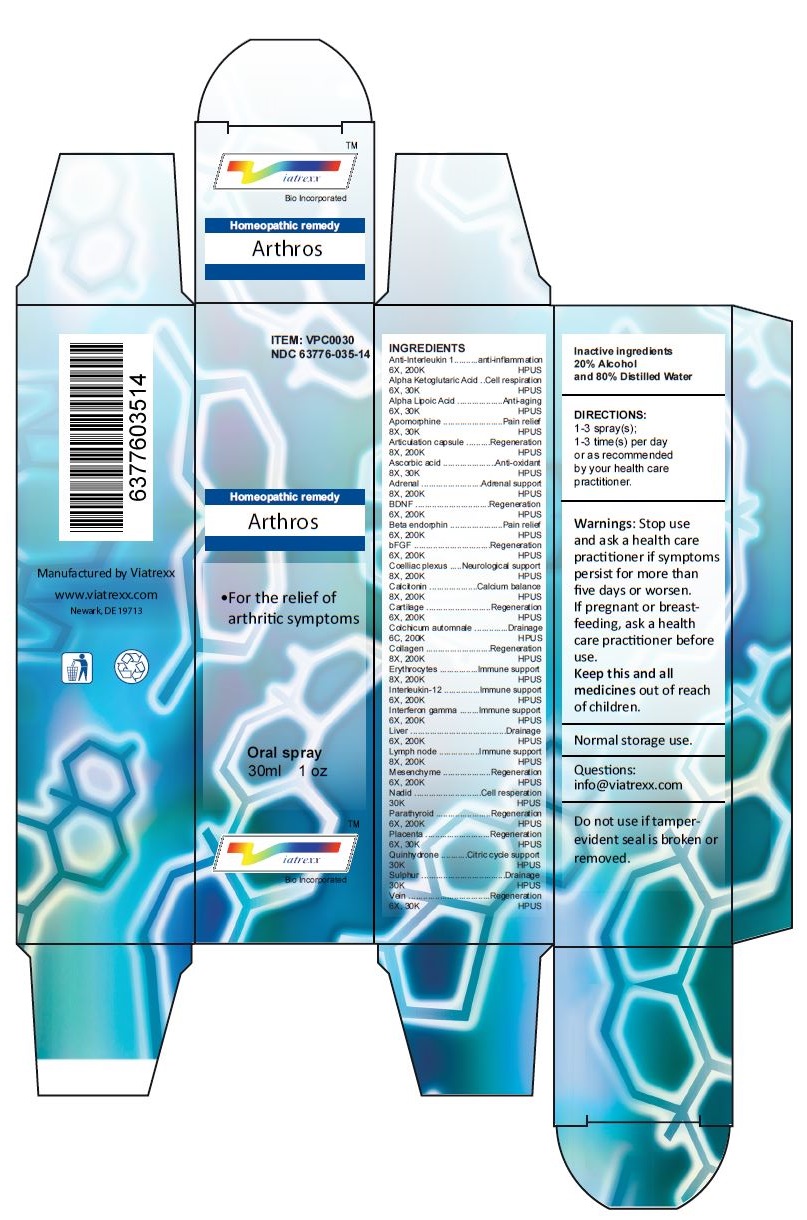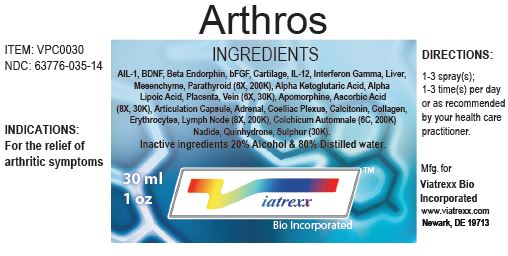 DRUG LABEL: Arthros
NDC: 63776-035 | Form: SPRAY
Manufacturer: VIATREXX BIO INCORPORATED
Category: homeopathic | Type: HUMAN OTC DRUG LABEL
Date: 20230110

ACTIVE INGREDIENTS: ANTI-INTERLEUKIN-1.ALPHA. IMMUNOGLOBULIN G RABBIT 200 [kp_C]/1 mL; .ALPHA.-KETOGLUTARIC ACID 30 [kp_C]/1 mL; .ALPHA.-LIPOIC ACID 30 [kp_C]/1 mL; APOMORPHINE 30 [kp_C]/1 mL; BOS TAURUS JOINT CAPSULE 200 [kp_C]/1 mL; SUS SCROFA JOINT CAPSULE 200 [kp_C]/1 mL; ASCORBIC ACID 30 [kp_C]/1 mL; BOS TAURUS ADRENAL GLAND 200 [kp_C]/1 mL; SUS SCROFA ADRENAL GLAND 200 [kp_C]/1 mL; BRAIN-DERIVED NEUROTROPHIC FACTOR HUMAN 200 [kp_C]/1 mL; METENKEFALIN 200 [kp_C]/1 mL; ERSOFERMIN 200 [kp_C]/1 mL; BOS TAURUS SOLAR PLEXUS 200 [kp_C]/1 mL; SUS SCROFA SOLAR PLEXUS 200 [kp_C]/1 mL; CALCITONIN 200 [kp_C]/1 mL; BOS TAURUS CARTILAGE 200 [kp_C]/1 mL; SUS SCROFA CARTILAGE 200 [kp_C]/1 mL; COLCHICUM AUTUMNALE BULB 200 [kp_C]/1 mL; PORK COLLAGEN 200 [kp_C]/1 mL; BOS TAURUS RED BLOOD CELL 200 [kp_C]/1 mL; SUS SCROFA RED BLOOD CELL 200 [kp_C]/1 mL; EDODEKIN ALFA 200 [kp_C]/1 mL; INTERFERON GAMMA-1A 200 [kp_C]/1 mL; BEEF LIVER 200 [kp_C]/1 mL; PORK LIVER 200 [kp_C]/1 mL; BOS TAURUS LYMPH 200 [kp_C]/1 mL; SUS SCROFA LYMPH 200 [kp_C]/1 mL; BOS TAURUS MESENCHYME 200 [hp_Q]/1 mL; SUS SCROFA MESENCHYME 200 [hp_Q]/1 mL; NADIDE 30 [kp_C]/1 mL; BOS TAURUS PARATHYROID GLAND 200 [kp_C]/1 mL; SUS SCROFA PARATHYROID GLAND 200 [kp_C]/1 mL; BOS TAURUS PLACENTA 30 [kp_C]/1 mL; QUINHYDRONE 30 [kp_C]/1 mL; SULFUR 30 [kp_C]/1 mL; BOS TAURUS VEIN 30 [kp_C]/1 mL; SUS SCROFA VEIN 30 [kp_C]/1 mL
INACTIVE INGREDIENTS: ALCOHOL; WATER

Arthros

Active Ingredients

Anti-Interleukin 1 (6X, 200K), Alpha Ketoglutaric Acid (6X, 30K), Alpha Lipoic Acid (6X, 30K), Apomorphine (8X, 30K), Articulation capsule (8X, 200K), Ascorbic acid (8X, 30K), Adrenal (8X, 200K), BDNF (6X, 200K), Beta endorphin (6X, 200K), bFGF (6X, 200K), Coelliac plexus (8X, 200K), Calcitonin (8X, 200K), Cartilage (6X, 200K), Colchicum automnale (6C, 200K), Collagen (8X, 200K), Erythrocytes (8X, 200K), Interleukin-12 (6X, 200K), Interferon gamma (6X, 200K), Liver (6X, 200K), Lymph node (8X, 200K), Mesenchyme (6X, 200K), Nadid (30K), Parathyroid (6X, 200K), Placenta (6X, 30K), Quinhydrone (30K), Sulphur (30K), Vein (6X, 30K)

Purpose:

Anti-Interleukin 1 | Anti-inflammation
Alpha Ketoglutaric Acid | Cell respiration
Alpha Lipoic Acid | Anti-aging
Apomorphine | Pain relief
Articulation capsule | Regeneration
Ascorbic acid | Anti-oxidant
Adrenal | Adrenal support
BDNF | Regeneration
Beta endorphin | Pain relief
bFGF | Regeneration
Coelliac plexus | Neurological support
Calcitonin | Calcium balance
Cartilage | Regeneration
Colchicum automnale | Drainage
Collagen | Regeneration
Erythrocytes | Immune support
Interleukin-12 | Immune support
Interferon gamma | Immune support
Liver | Drainage
Lymph node | Immune support
Mesenchyme | Regeneration
Nadid | Cell respiration
Parathyroid | Regeneration
Placenta | Regeneration
Quinhydrone | Citric cycle support
Sulphur | Drainage
Vein | Regeneration

Uses

For the relief of arthritic symptoms

Warnings

Stop use and ask a health care practitioner if symptoms persist for more than five days or worsen. If pregnant or breastfeeding, ask a health care practitioner before use.

Dosage

1-3 spray(s); 1-3 time(s) per day or as recommended by your health care practitioner.

KEEP OUT OF REACH OF CHILDREN

Keep this and all medicines out of reach of children.

Inactive ingredients

20% Alcohol and 80% Water

Other Information

Normal storage use.
Do not use if tamper-evident seal is broken or removed.

Questions

info@viatrexx.com

Principal Display Panel

ITEM: VPC0030
NDC 63776-035-14
Homeopathic remedy
Arthros
• For the relief of arthritic symptoms
Oral spray
30ml 1 oz
Viatrexx™ Bio Incorporated
Manufactured by Viatrexx
www.viatrexx.com
Newark, DE 19713

Arthros
30 ml
1 oz
Viatrexx™ Bio Incorporated
ITEM: VPC0030
NDC: 63776-035-14
INDICATIONS:
For the relief of arthritic symptoms
DIRECTIONS:
1-3 spray(s); 1-3 time(s) per day or as recommended by your health care practitioner.
Mfg. for
Viatrexx Bio Incorporated
www.viatrexx.com
Newark, DE 19713